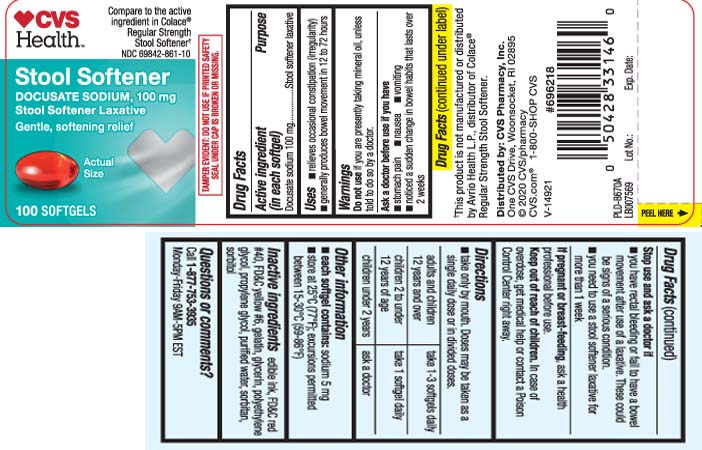 DRUG LABEL: Stool Softener
NDC: 69842-861 | Form: CAPSULE
Manufacturer: CVS Pharmacy
Category: otc | Type: HUMAN OTC DRUG LABEL
Date: 20240313

ACTIVE INGREDIENTS: DOCUSATE SODIUM 100 mg/1 1
INACTIVE INGREDIENTS: FD&C RED NO. 40; FD&C YELLOW NO. 6; GELATIN; SORBITAN; POLYETHYLENE GLYCOL, UNSPECIFIED; PROPYLENE GLYCOL; WATER; SORBITOL; GLYCERIN

DRUG FACTS

Active ingredient (in each softgel)

Docusate Sodium 100 mg

Purpose

Stool softener laxative

Uses

- relieves occasional constipation and irregularity
- generally produces bowel movement in 12 to 72 hours

Warnings

Do not use

if you are presently taking mineral oil, unless told to do so by a doctor.

Ask a doctor before use if

- stomach pain
- nausea
- vomiting
- noticed a sudden change in bowel habits that lasts over 2 weeks

Stop use and ask a doctor if

- you have rectal bleeding or fail to have a bowel movement after using a laxative. These could be a sign of a serious condition
- you need to use a laxative for more than 1 week

If pregnant or breast-feeding,

ask a health care professional before use.

Keep out of reach of children.

In case of overdose, get medical help or contact a Poison Control Center right away.

Directions

- take only by mouth. Doses may be taken as a single daily dose or in divided doses.

adults and children 12 over and over | take 1-3 softgels daily.
children 2 to under 12 years of age | take 1 softgel daily
children under 2 years | ask a doctor

Other information

- each softgel contains: sodium 5 mg
- store 25ºC (77ºF); excursion permitted between 15-30ºC (59-86ºF)

Inactive ingredients

edible ink, FD&C Red #40, FD&C Yellow #6, gelatin, glycerin, polyethylene glycol, propylene glycol, purified water sorbitan, sorbitol

Questions or comments?

Call 1-877-753-3935 Monday-Friday 9AM-5PM EST

Principal Display Panel

Compare to the active ingredient in Colace® Regular Strength Stool Softener†

Stool Softener

DOCUSATE SODIUM, 100 mg

Stool Softener Laxative

Gentle, softener relief

SOFTGELS

†This product is not manufactured or distributed by Avrio HealthL.P., distributor of Colace® Regular Strength Stool Softener.

TAMPER EVIDENT: DO NOT USE IF PRINTED SAFETY SEAL UNDER CAP IS BROKEN OR MISSING.

Distributed by: CVS Pharmacy, Inc.

One CVS Drive, Woonsocket, RI 02895

Product Label

CVS HEALTH Stool Softener